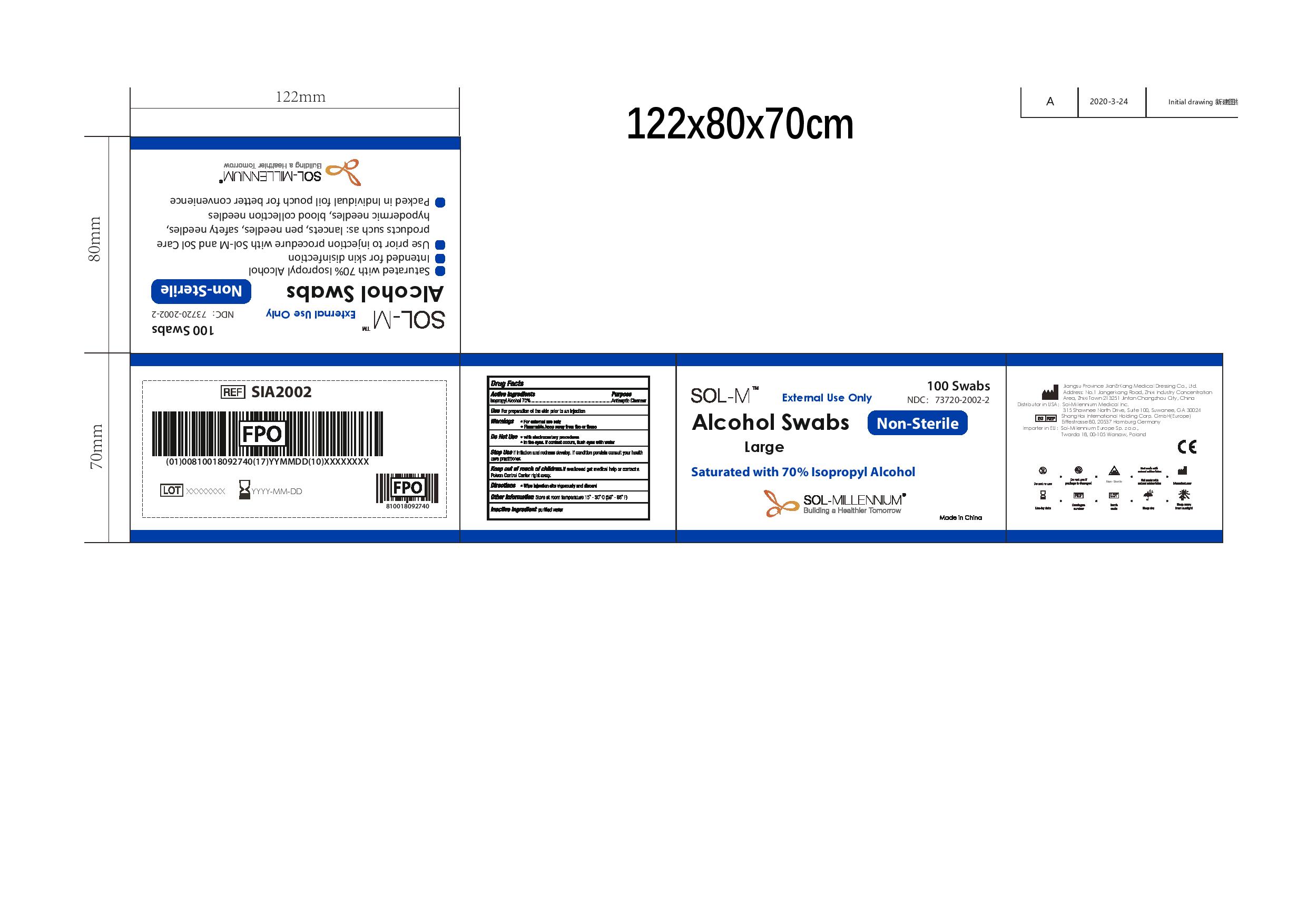 DRUG LABEL: Sol-M Alcohol Swabs Large Non-Sterile
NDC: 73720-2002 | Form: SWAB
Manufacturer: Sol-Millennium Medical Inc
Category: otc | Type: HUMAN OTC DRUG LABEL
Date: 20220622

ACTIVE INGREDIENTS: ISOPROPYL ALCOHOL 0.7 mL/1 mL
INACTIVE INGREDIENTS: WATER

Sol-M Alcohol Swabs Large Non-Sterile Box

Active ingredients

Isopropyl Alcohol 70%

Purpose

Isopropyl Alcohol 70%................Antiseptic Cleanser

Use

For preparation of the skin prior to an injection

WARNINGS

- For external use only
- Flammable, keep away from fire or flame

DO NOT USE

- with electrocautery procedures
- In the eyes. If contact occurs, flush eyes with water

STOP USE

If irritation and redness develop. If condition persists consult your health care practitioner.

KEEP OUT OF REACH OF CHILDREN

If swallowed get medical help or contact a Poison Control Center right away.

Directions

- Wipe injection site vigorously and discard

Other information

Store at room temperature 15 - 30 C (59 - 86 F)

Inactive ingredient

purified water

PACKAGE LABEL

100 Swabs

External Use Only

NDC: 73720-2002-2

Sol-M Alcohol Swabs Non-Sterile Large

Saturated with 70% Isopropyl Alcohol

Sol-Millennium

Building a Healthier Tomorrow

Made in China